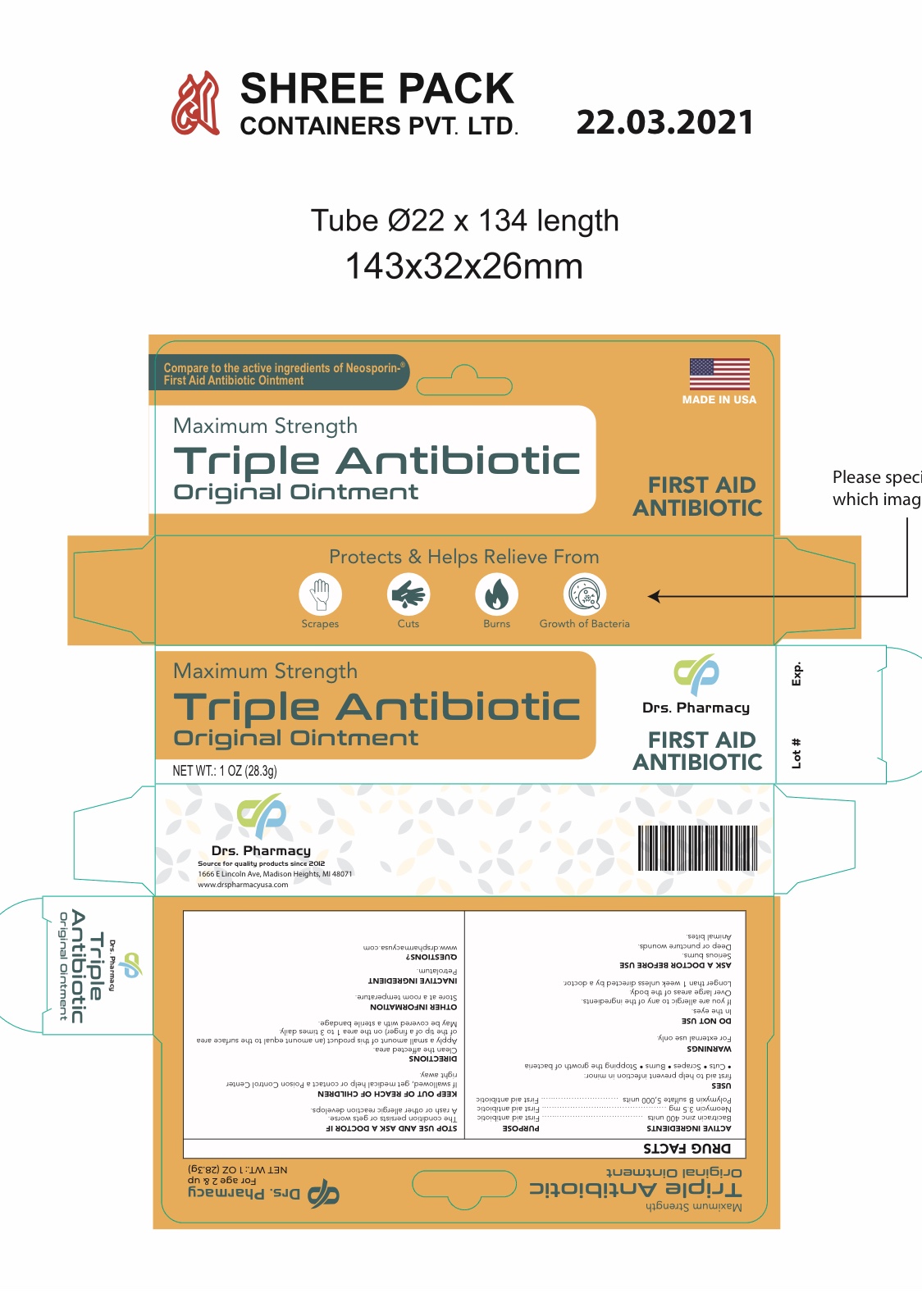 DRUG LABEL: Drs. pharmacy triple antibiotic
NDC: 80489-012 | Form: OINTMENT
Manufacturer: OL PHARMA TECH, LLC
Category: otc | Type: HUMAN OTC DRUG LABEL
Date: 20250109

ACTIVE INGREDIENTS: NEOMYCIN SULFATE 3.5 mg/1 g; BACITRACIN ZINC 400 [USP'U]/1 g; POLYMYXIN B SULFATE 5000 [USP'U]/1 g
INACTIVE INGREDIENTS: PETROLATUM

Active Ingredients

- Bacitracin Zinc 400 units
- Neomycin Sulfate 3.5mg
- Polymyxin B Sulfate 5,000 units

Purpose

- First aid antibiotic

Uses

First aid to help prevent infection in minor:

- cuts
- scrapes
- burns

Warnings

For external use only

Ask a doctor before use if you have

- serious burns
- deep or puncture wounds
- animal bites

Stop use and ask a doctor if

- condition persists or gets worse
- rash or other allergic reaction develops

- do not use in the eyes
- do not apply over large areas of the body
- if you are allergic to any of the ingredients
- longer than one week unless directed by your doctor

keep out of the reach of children

If swallowed, get medical help or contact a Poison Control Center right away

Directions

- clean the affected area
- apply a small amount of this product (an amount equal tot the surface area of the tip of a finer) on the area 1 to 3 times daily
- may be covered with a sterile bandage

OTHER SAFETY INFORMATION

- store at room temperature

Inactive ingredient

Petrolatum

Questions

www.drspharmacyusa.com

Principal display panel

Maximum Strength